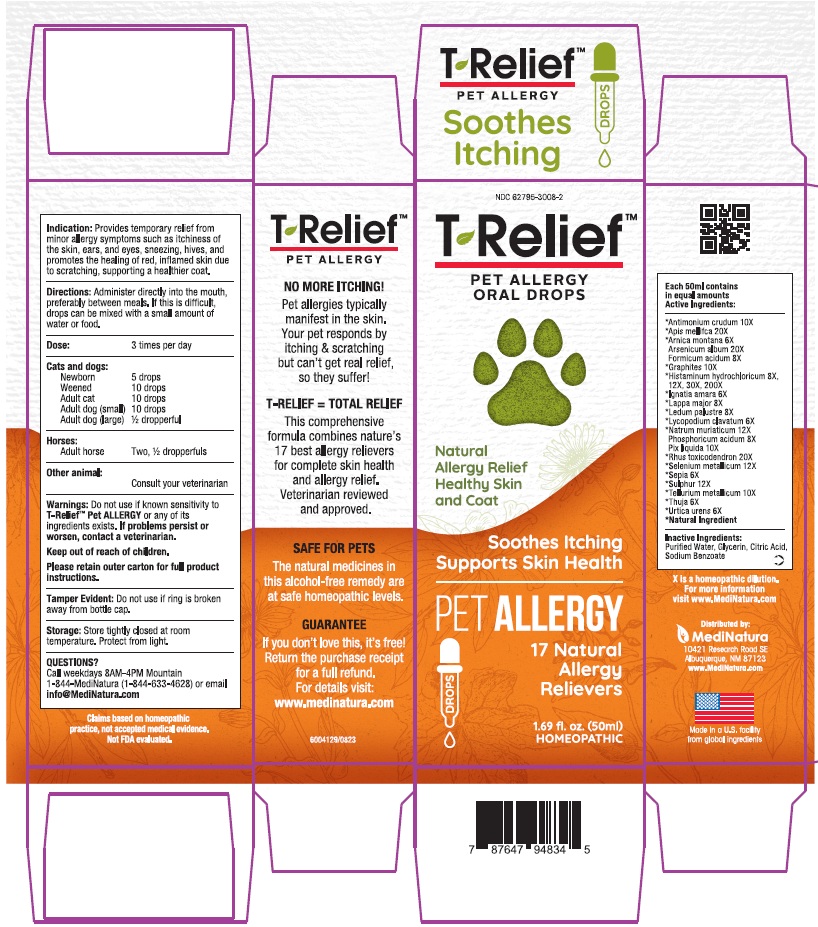 DRUG LABEL: T Relief Pet Allergy
NDC: 62795-3008 | Form: SOLUTION/ DROPS
Manufacturer: MediNatura New Mexico Inc
Category: homeopathic | Type: OTC ANIMAL DRUG LABEL
Date: 20251228

ACTIVE INGREDIENTS: ANTIMONY TRISULFIDE 10 [hp_X]/50 mL; APIS MELLIFERA 20 [hp_X]/50 mL; Arnica montana 6 [hp_X]/50 mL; ARSENIC TRIOXIDE 20 [hp_X]/50 mL; FORMIC ACID 8 [hp_X]/50 mL; GRAPHITE 10 [hp_X]/50 mL; HISTAMINE DIHYDROCHLORIDE 8 [hp_X]/50 mL; STRYCHNOS IGNATII SEED 6 [hp_X]/50 mL; ARCTIUM LAPPA ROOT 8 [hp_X]/50 mL; RHODODENDRON TOMENTOSUM LEAFY TWIG 8 [hp_X]/50 mL; LYCOPODIUM CLAVATUM SPORE 6 [hp_X]/50 mL; SODIUM CHLORIDE 12 [hp_X]/50 mL; PHOSPHORIC ACID 8 [hp_X]/50 mL; PINE TAR 10 [hp_X]/50 mL; TOXICODENDRON PUBESCENS SHOOT 20 [hp_X]/50 mL; SELENIUM 12 [hp_X]/50 mL; SEPIA OFFICINALIS JUICE 6 [hp_X]/50 mL; SULFUR 12 [hp_X]/50 mL; TELLURIUM 10 [hp_X]/50 mL; THUJA OCCIDENTALIS LEAFY TWIG 6 [hp_X]/50 mL; URTICA URENS WHOLE 6 [hp_X]/50 mL
INACTIVE INGREDIENTS: WATER; GLYCERIN; CITRIC ACID ACETATE; Sodium Benzoate

T Relief Pet Allergy

Warnings

Do not use if known sensitivity to
T-Relief™ Pet ALLERGY or any of its
ingredients exists. If problems persist or
worsen, contact a veterinarian.
Keep out of reach of children.
Please retain outer carton for full product
instructions.

Indication:

Provides temporary relief from
minor allergy symptoms such as itchiness of
the skin, ears, and eyes, sneezing, hives, and
promotes the healing of red, inflamed skin due
to scratching, supporting a healthier coat.

Directions:

Administer directly into the mouth,
preferably between meals. If this is difficult,
drops can be mixed with a small amount of
water or food.
Dose: 3 times per day
Cats and dogs:
Newborn 5 drops
Weened 10 drops
Adult cat 10 drops
Adult dog (small) 10 drops
Adult dog (large) ½ dropperful
Horses:
Adult horse Two, ½ dropperfuls
Other animal:
Consult your veterinarian

Inactive Ingredients:

Purified Water, Glycerin, Citric Acid,
Sodium Benzoate

Keep out of reach of children

Purpose

Soothes Itching
Supports Skin Health

Actives

Each 50ml contains
in equal amounts
Active Ingredients:
*Antimonium crudum 10X
*Apis mellifca 20X
*Arnica montana 6X
Arsenicum album 20X
Formicum acidum 8X
*Graphites 10X
*Histaminum hydrochloricum 8X,
12X, 30X, 200X
*Ignatia amara 6X
*Lappa major 8X
*Ledum palustre 8X
*Lycopodium clavatum 6X
*Natrum muriaticum 12X
Phosphoricum acidum 8X
Pix liquida 10X
*Rhus toxicodendron 20X
*Selenium metallicum 12X
*Sepia 6X
*Sulphur 12X
*Tellurium metallicum 10X
*Thuja 6X
*Urtica urens 6X
*Natural Ingredient

PACKAGE LABEL

Add image transcription here...